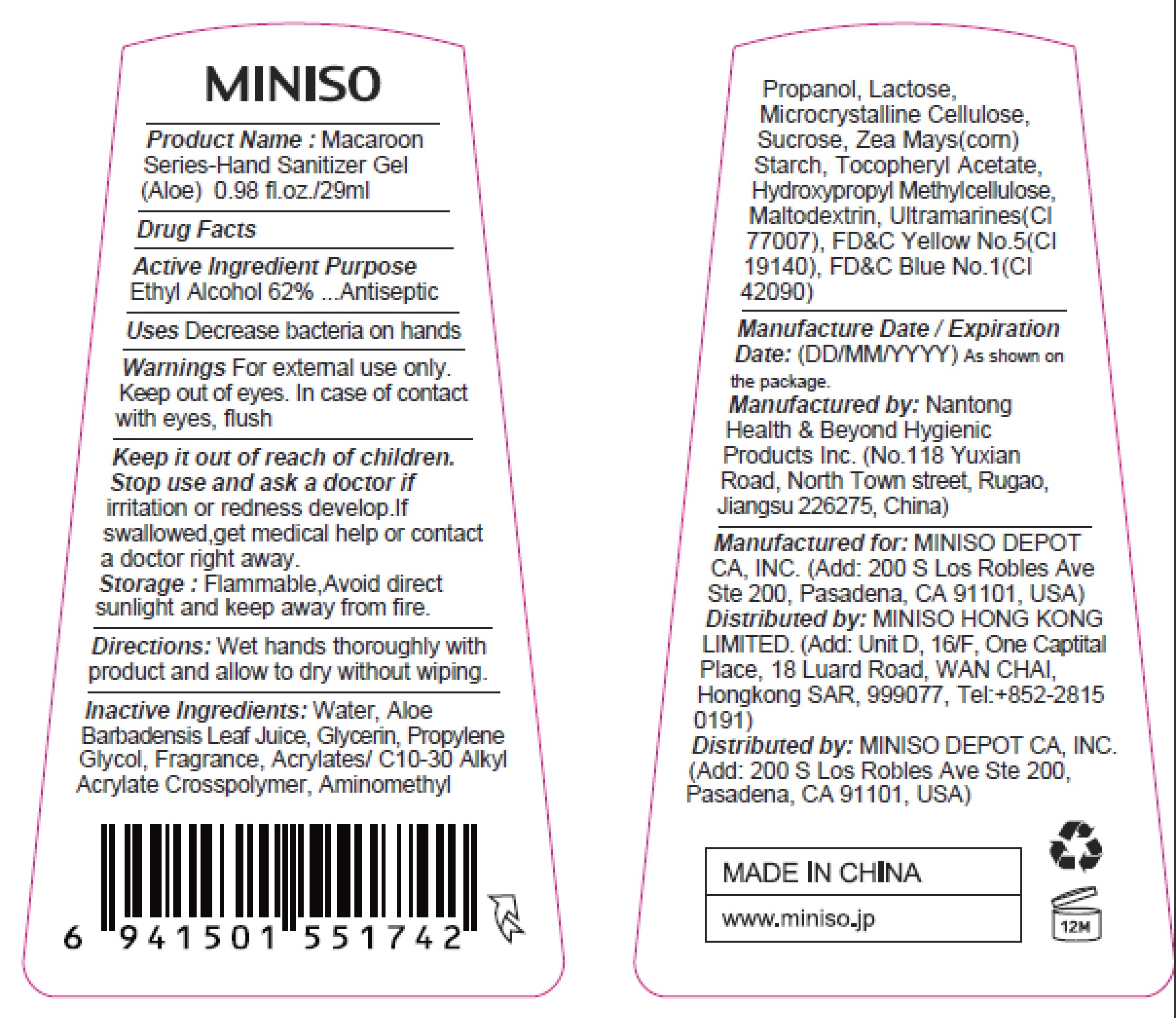 DRUG LABEL: Hand Sanitizer
NDC: 73950-006 | Form: GEL
Manufacturer: MINISO DEPOT CA, INC.
Category: otc | Type: HUMAN OTC DRUG LABEL
Date: 20200525

ACTIVE INGREDIENTS: ALCOHOL 62 mL/100 mL
INACTIVE INGREDIENTS: FD&C YELLOW NO. 5; ULTRAMARINE BLUE; AMINOMETHYLPROPANOL; FD&C BLUE NO. 1; HYPROMELLOSE, UNSPECIFIED; .ALPHA.-LACTOSE; SUCROSE; MALTODEXTRIN; ALOE VERA LEAF; PROPYLENE GLYCOL; WATER; GLYCERIN; CARBOMER INTERPOLYMER TYPE A (55000 CPS); .ALPHA.-TOCOPHEROL ACETATE; STARCH, CORN; MICROCRYSTALLINE CELLULOSE

Active Ingredient
Ethyl Alcohol 62%

Purpose
Antiseptic

INDICATIONS AND USAGE

Uses Decrease bacteria on hands

Warnings For external use only.

Keep out of eyes. In case of contact with eyes, flush

Keep it out of reach of children.

Stop use and ask a doctor if irritation or redness develop.If swallowed,get medical help or contact a doctor right away.

STORAGE AND HANDLING

Storage: Flammable,Avoid direct sunlight and keep away from fire.

DOSAGE AND ADMINISTRATION

Directions: Wet hands thoroughly with product and allow to dry without wiping.

Inactive Ingredients:

Water, Aloe Barbadensis Leaf Juice, Glycerin, Propylene Glycol, Fragrance, Acrylates/ C10-30 Alkyl Acrylate Crosspolymer, Aminomethyl Propanol， Lactose, Microcrystalline Cellulose, Sucrose, Zea Mays(corn) Starch, Tocopheryl Acetate, Hydroxypropyl Methylcellulose, Maltodextrin, Ultramarines(CI77007), FD&C Yellow No.5(CI19140), FD&C Blue No.1(CI42090)